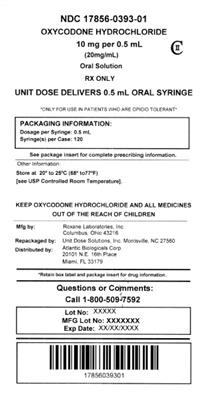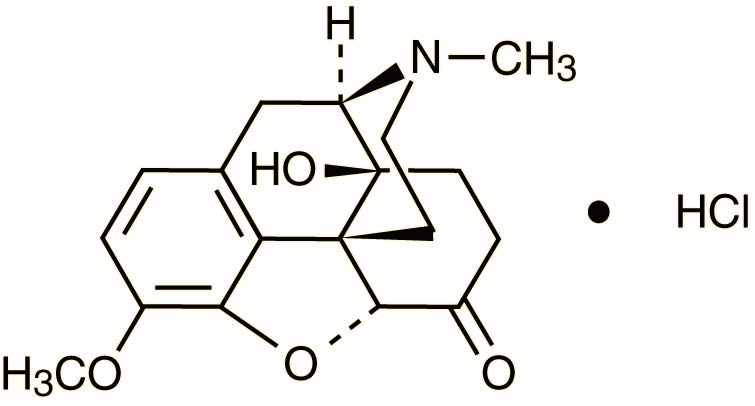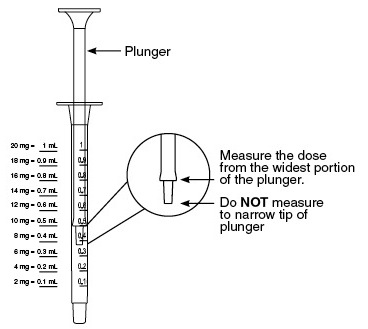 DRUG LABEL: Oxycodone Hydrochloride
NDC: 17856-0393 | Form: SOLUTION
Manufacturer: Atlantic Biologicals Corps
Category: prescription | Type: HUMAN PRESCRIPTION DRUG LABEL
Date: 20160629
DEA Schedule: CII

ACTIVE INGREDIENTS: OXYCODONE HYDROCHLORIDE 100 mg/5 mL
INACTIVE INGREDIENTS: ANHYDROUS CITRIC ACID; EDETATE DISODIUM; D&C YELLOW NO. 10; WATER; SODIUM BENZOATE; SORBITOL; SUCRALOSE

HIGHLIGHTS OF PRESCRIBING INFORMATION

These highlights do not include all the information needed to use OXYCODONE HYDROCHLORIDE Oral Solution USP safely and effectively. See full prescribing information for OXYCODONE HYDROCHLORIDE Oral Solution USP. OXYCODONE HYDROCHLORIDE Oral Solution USP, for oral use, CII Initial U.S. Approval: 1950

WARNING: RISK OF MEDICATION ERRORS

See full prescribing information for complete boxed warning

Oxycodone Hydrochloride Oral Solution USP, 100 mg per 5 mL (20 mg/mL) is available in one concentration, as 20 mg oxycodone hydrochloride per mL of solution. The 100 mg per 5 mL (20 mg/mL) concentration is indicated for use in opioid-tolerant patients only.

Take care to avoid dosing errors due to confusion between mg and mL, and other oxycodone solutions with different concentrations, which could result in accidental overdose and death. (5.1)

Keep Oxycodone Hydrochloride Oral Solution USP out of the reach of children.

1 INDICATIONS AND USAGE

Oxycodone Hydrochloride Oral Solution USP, 20 mg per mL solution is an opioid agonist indicated for the management of moderate to severe acute and chronic pain in opioid-tolerant patients. (1)

2 DOSAGE AND ADMINISTRATION

- Oxycodone hydrochloride oral solution: 5 to 15 mg every 4 to 6 hours as needed. (2.2).

3 DOSAGE FORMS AND STRENGTHS

Oral Solution 100 mg per 5 mL (20 mg/mL): Each mL contains 20 mg of oxycodone hydrochloride. (3)

4 CONTRAINDICATIONS

- Respiratory depression in the absence of resuscitative equipment. (4)
- Paralytic ileus. (4)
- Acute or severe bronchial asthma or hypercarbia. (4)
- Known hypersensitivity to oxycodone. (4)

5 WARNINGS AND PRECAUTIONS

- Risk of Medication Errors: Use caution when prescribing, dispensing, and administering to avoid dosing errors due to confusion between different concentrations and between mg and mL, which could result in accidental overdose and death. (5.1)
- Respiratory depression: Increased risk in elderly, debilitated patients, those suffering from conditions accompanied by hypoxia, hypercapnia, or upper airway obstruction. (5.2)
- Misuse, Abuse and Diversion: Oxycodone hydrochloride is a Schedule II controlled substance with an abuse liability similar to other opioids. (5.3)
- CNS effects: Additive CNS depressive effects when used in conjunction with alcohol, other opioids, or illicit drugs. (5.4)
- Elevation of intracranial pressure: May be markedly exaggerated in the presence of head injury, other intracranial lesions. (5.5)
- Hypotensive effect: Increased risk with compromised ability to maintain blood pressure. (5.6)
- Prolonged gastric obstruction: In patients with gastrointestinal obstruction, especially paralytic ileus. (5.7)
- Sphincter of Oddi spasm and diminished biliary/pancreatic secretions. Increased risk with biliary tract disease. (5.8)
- Special Risk Groups: Use with caution and in reduced dosages in patients with severe renal or hepatic impairment, Addison’s disease, hypothyroidism, prostatic hypertrophy, or urethral stricture, elderly, CNS depression, toxic psychosis, acute alcoholism and delirium tremens, may aggravate or induce seizures. (5.9)
- Impaired mental/physical abilities: Caution must be used with potentially hazardous activities. (5.10)
- Concomitant use of CYP3A4 inhibitors may increase opioid effects (5.11)

6 ADVERSE REACTIONS

Most common adverse reactions are nausea, constipation, vomiting, headache, pruritus, insomnia, dizziness, asthenia, and somnolence. (6)

To report SUSPECTED ADVERSE REACTIONS, contact Roxane Laboratories, Inc at 800-962-8364 or FDA at 1-800-FDA-1088 or www.fda.gov/medwatch

7 DRUG INTERACTIONS

- CNS depressants: Increased risk of respiratory depression, hypotension, profound sedation, or coma. Use with caution in reduced dosages. (7.1)
- Muscle relaxants: Enhance the neuromuscular blocking action of skeletal muscle relaxants and produce an increased degree of respiratory depression. (7.2)
- Mixed agonist/antagonist opioid analgesics (i.e. pentazocine, nalbuphine, and butorphanol): May reduce the analgesic effect and/or may precipitate withdrawal symptoms. (7.3)
- The CYP3A4 enzyme plays a major role in the metabolism of oxycodone, drugs that inhibit CYP3A4 activity may cause decreased clearance of oxycodone which could lead to an increase in oxycodone plasma concentrations. (7.4)
- Monoamine oxidase inhibitors (MAOIs): No specific interaction has been observed but caution in the use of oxycodone hydrochloride in patients taking this class of drugs is appropriate. (7.5)

8 USE IN SPECIFIC POPULATIONS

- Geriatric patients (8.5), Renal impairment (8.7): Use caution during dose selection, starting at the low end of the dosing range while carefully monitoring for side effects.
- Hepatic impairment (8.6): initiate therapy at 1/3 to 1/2 the usual doses and titrate carefully.

FULL PRESCRIBING INFORMATION

WARNING: RISK OF MEDICATION ERRORS

Oxycodone Hydrochloride Oral Solution USP is available as a 100 mg per 5 mL (20 mg/mL) concentration and is indicated for use in opioid-tolerant patients only.

Take care when prescribing and administering Oxycodone Hydrochloride Oral Solution USP to avoid dosing errors due to confusion between mg and mL, and other oxycodone solutions with different concentrations, which could result in accidental overdose and death. Take care to ensure the proper dose is communicated and dispensed.

Keep Oxycodone Hydrochloride Oral Solution USP out of the reach of children. In case of accidental ingestion, seek emergency medical help immediately.

1 INDICATIONS AND USAGE

Oxycodone Hydrochloride Solution USP, 100 mg per 5 mL () is an opioid analgesic indicated for the management of moderate to severe acute and chronic pain in opioid-tolerant patients. Oral 20 mg/mL

Oxycodone Hydrochloride Oral Solution USP, 100 mg per 5 mL (20 mg/mL) may cause fatal respiratory depression when administered to patients not previously exposed to opioids. Patients considered to be opioid tolerant are those who are taking at least 30 mg of oral oxycodone per day, or at least 60 mg oral morphine per day, or at least 12 mg hydromorphone per day, or an equianalgesic dose of another opioid, for a week or longer.

2 DOSAGE AND ADMINISTRATION

Take care when prescribing and administering oxycodone hydrochloride oral solution to avoid dosing errors due to confusion between mg and mL, which could result in accidental overdose and death. Take care to ensure the proper dose is communicated and dispensed. When writing prescriptions, include both the total dose in mg and the total dose in volume. Always use the enclosed calibrated oral syringe when administering oxycodone hydrochloride oral solution, 100 mg per 5 mL (20 mg/mL), to ensure the dose is measured and administered accurately.

Selection of patients for treatment with oxycodone hydrochloride should be governed by the same principles that apply to the use of similar opioid analgesics. Individualize treatment in every case, using non-opioid analgesics, opioids on an as needed basis and/or combination products, and chronic opioid therapy in a progressive plan of pain management such as outlined by the World Health Organization, the Agency for Healthcare Research and Quality, and the American Pain Society.

2.2 Conversion to Oral Oxycodone Hydrochloride

The 100 mg per 5 mL (20 mg/mL) oral solution formulation is for use in opioid-tolerant patients only who have already been receiving opioid therapy. Use this strength only for patients that have already been titrated to a stable analgesic regimen using lower strengths of oxycodone hydrochloride and who can benefit from use of a smaller volume of oral solution.

There is inter-patient variability in the potency of opioid drugs and opioid formulations. Therefore, a conservative approach is advised when determining the total daily dose of oxycodone hydrochloride. It is better to underestimate a patient’s 24-hour oral oxycodone hydrochloride dose and make available rescue medication than to overestimate the 24-hour oral oxycodone hydrochloride dose and manage an adverse experience of overdose.

Consider the following general points regarding opioid conversions.

Conversion From Non-Oxycodone Opioids to Oral Oxycodone Hydrochloride.

In converting patients from other opioids to oxycodone hydrochloride, close observation and adjustment of dosage based upon the patient’s response to oxycodone hydrochloride is imperative. Physicians and other healthcare professionals are advised to refer to published relative potency information, keeping in mind that conversion ratios are only approximate.

Conversion From Controlled-Release Oral Oxycodone to Oral Oxycodone Hydrochloride.

The relative bioavailability of oxycodone hydrochloride oral solution compound to controlled-release oxycodone is unknown. The extended duration of release of oxycodone hydrochloride from controlled-release tablets results in reduced maximum and increased minimum plasma oxycodone hydrochloride concentrations than with shorter acting oxycodone hydrochloride products. Conversion from controlled-release tablets could lead to excessive sedation at peak serum levels. Therefore, dosage adjustment with close observation is necessary.

Conversion From Oral Oxycodone Hydrochloride to Controlled-Release Oral Oxycodone

The relative bioavailability of oxycodone hydrochloride oral solution compared to controlled-release oxycodone is unknown, so conversion to controlled-release tablets must be accompanied by close observation for signs of excessive sedation.

2.3 Maintenance of Therapy

Continual reevaluation of the patient receiving oxycodone hydrochloride is important, with special attention to the maintenance of pain management and the relative incidence of side effects associated with therapy. If the level of pain increases, effort should be made to identify the source of increased pain, while adjusting the dose as described above to decrease the level of pain. During chronic therapy, especially for non-cancer-related pain (or pain associated with other terminal illnesses), periodically reassess the continued need for the use of opioid analgesics.

2.4 Cessation of Therapy

When a patient no longer requires therapy with oxycodone hydrochloride gradually taper the dose to prevent signs and symptoms of withdrawal in the physically dependent patient.

3 DOSAGE FORMS AND STRENGTHS

The 100 mg per 5 mL (20 mg/mL) strength: Each 5 mL of clear, light yellow to yellow oxycodone hydrochloride oral solution contains oxycodone hydrochloride 100 mg. The concentration of this solution is 20 mg/mL.

4 CONTRAINDICATIONS

Oxycodone Hydrochloride Oral Solution USP is contraindicated in patients with respiratory depression in the absence of resuscitative equipment.

Oxycodone Hydrochloride Oral Solution USP is contraindicated in any patient who has or is suspected of having paralytic ileus.

Oxycodone Hydrochloride Oral Solution USP is contraindicated in patients with acute or severe bronchial asthma or hypercarbia.

Oxycodone Hydrochloride Oral Solution USP is contraindicated in patients with known hypersensitivity to oxycodone, oxycodone salts, or any components of the product.

5 WARNINGS AND PRECAUTIONS

5.1 Risk of Medication Errors

Oxycodone hydrochloride oral solution is available in 100 mg per 5 mL (20 mg/mL) concentration. Use caution when prescribing, dispensing, and administering oxycodone hydrochloride oral solution to avoid dosing errors due to confusion between mg and mL, and other oxycodone solutions with different concentrations, which could result in accidental overdose and death. Use caution to ensure the dose is communicated clearly and dispensed accurately. Always use the enclosed calibrated syringe when administering oxycodone hydrochloride oral solution 100 mg per 5 mL (20 mg/mL) to ensure the dose is measured and administered accurately.

5.2 Respiratory Depression

Respiratory depression is the primary risk of oxycodone hydrochloride. Respiratory depression occurs more frequently in elderly or debilitated patients and in those suffering from conditions accompanied by hypoxia, hypercapnia, or upper airway obstruction, in whom even moderate therapeutic doses may significantly decrease pulmonary ventilation.

Use oxycodone hydrochloride with extreme caution in patients with chronic obstructive pulmonary disease or cor pulmonale and in patients having a substantially decreased respiratory reserve (e.g., severe kyphoscoliosis), hypoxia, hypercapnia, or preexisting respiratory depression. In such patients, even usual therapeutic doses of oxycodone hydrochloride may increase airway resistance and decrease respiratory drive to the point of apnea. Consider alternative non-opioid analgesics, and use oxycodone hydrochloride only under careful medical supervision at the lowest effective dose in such patients.

Oxycodone hydrochloride 100 mg per 5 mL (20 mg/mL) oral solution is for use in . Administration of this formulation may cause fatal respiratory depression when administered to patients who are not tolerant to the respiratory depressant effects of opioids. opioid-tolerant patients only

5.3 Misuse, Abuse and Diversion of Opioids

Oxycodone hydrochloride is an opioid agonist and a Schedule II controlled substance. Such drugs are sought by drug abusers and people with addiction disorders. Diversion of Schedule II products is an act subject to criminal penalty.

Oxycodone hydrochloride can be abused in a manner similar to other opioid agonists, legal or illicit. This should be considered when prescribing or dispensing oxycodone hydrochloride in situations where the physician or pharmacist is concerned about an increased risk of misuse, abuse, or diversion.

Oxycodone hydrochloride may be abused by crushing, chewing, snorting or injecting the product. These practices pose a significant risk to the abuser that could result in overdose and death. [See Drug Abuse and Dependence (9)]

Concerns about abuse, addiction, and diversion should not prevent the proper management of pain. Healthcare professionals should contact their State Professional Licensing Board or State Controlled Substances Authority for information on how to prevent and detect abuse or diversion of this product.

5.4 Interactions with Alcohol and Drugs of Abuse

Oxycodone hydrochloride may be expected to have additive effects when used in conjunction with alcohol, other opioids, or illicit drugs that cause central nervous system depression because respiratory depression, hypotension, profound sedation, coma or death may result.

5.5 Use In Head Injury and Increased Intracranial Pressure

In the presence of head injury, intracranial lesions or a preexisting increase in intracranial pressure, the possible respiratory depressant effects of oxycodone hydrochloride and its potential to elevate cerebrospinal fluid pressure (resulting from vasodilation following CO retention) may be markedly exaggerated. Furthermore, oxycodone hydrochloride can produce effects on pupillary response and consciousness, which may obscure neurologic signs of further increases in intracranial pressure in patients with head injuries.2

5.6 Hypotensive Effect

Oxycodone hydrochloride may cause severe hypotension in an individual whose ability to maintain blood pressure has already been compromised by a depleted blood volume or concurrent administration of drugs such as phenothiazines or general anesthetics. Oxycodone hydrochloride may produce orthostatic hypotension and syncope in ambulatory patients.

Administer oxycodone hydrochloride with caution to patients in circulatory shock, as vasodilation produced by the drug may further reduce cardiac output and blood pressure.

5.7 Gastrointestinal Effects

Do not administer oxycodone hydrochloride to patients with gastrointestinal obstruction, especially paralytic ileus because oxycodone hydrochloride diminishes propulsive peristaltic waves in the gastrointestinal tract and may prolong the obstruction.

The administration of oxycodone hydrochloride may obscure the diagnosis or clinical course in patients with acute abdominal condition.

5.8 Use In Pancreatic/Biliary Tract Disease

Use oxycodone hydrochloride with caution in patients with biliary tract disease, including acute pancreatitis, as oxycodone hydrochloride may cause spasm of the sphincter of Oddi and diminish biliary and pancreatic secretions.

5.9 Special Risk Groups

Use oxycodone hydrochloride with caution and in reduced dosages in patients with severe renal or hepatic impairment, Addison’s disease, hypothyroidism, prostatic hypertrophy, or urethral stricture, and in elderly or debilitated patients. [See Use in Specific Populations (8.5)]

Exercise caution in the administration of oxycodone hydrochloride to patients with CNS depression, toxic psychosis, acute alcoholism and delirium tremens. All opioids may aggravate convulsions in patients with convulsive disorders, and all opioids may induce or aggravate seizures in some clinical settings.

Keep oxycodone hydrochloride oral solution out of the reach of children. In case of accidental ingestion, seek emergency medical help immediately.

5.10 Driving and Operating Machinery

Caution patients that oxycodone hydrochloride could impair the mental and/or physical abilities needed to perform potentially hazardous activities such as driving a car or operating machinery.

Caution patients about the potential combined effects of oxycodone hydrochloride with other CNS depressants, including other opioids, phenothiazines, sedative/hypnotics and alcohol. [See Drug Interactions (7)]

5.11 Cytochrome P450 3A4 Inhibitors and Inducers

Since the CYP3A4 isoenzyme plays a major role in the metabolism of oxycodone, drugs that alter CYP3A4 activity may cause changes in clearance of oxycodone which could lead to changes in oxycodone plasma concentrations. The expected clinical results with CYP3A4 inhibitors would be an increase in oxycodone plasma concentrations and possibly increased or prolonged opioid effects. The expected clinical results with CYP3A4 inducers would be a decrease in oxycodone plasma concentrations, lack of efficacy or, possibly, development of an abstinence syndrome in a patient who had developed physical dependence to oxycodone.

If co-administration is necessary, caution is advised when initiating oxycodone treatment in patients currently taking, or discontinuing, CYP3A4 inhibitors or inducers. Evaluate these patients at frequent intervals and consider dose adjustments until stable drug effects are achieved. [Drug Interactions (7.4) and Clinical Pharmacology (12.3)]

6 ADVERSE REACTIONS

Serious adverse reactions that may be associated with oxycodone therapy in clinical use are those observed with other opioid analgesics and include: respiratory depression, respiratory arrest, circulatory depression, cardiac arrest, hypotension, and/or shock.

The common adverse events seen on initiation of therapy with oxycodone are also typical opioid side effects. These events are dose dependent, and their frequency depends on the clinical setting, the patient’s level of opioid tolerance, and host factors specific to the individual. They should be expected and managed as a part of opioid therapy. The most frequent adverse events include nausea, constipation, vomiting, headache, and pruritus.

The frequency of adverse events during initiation of opioid therapy may be minimized by careful individualization of starting dosage, slow titration and the avoidance of large rapid swings in plasma concentration of the opioid. Many of these common adverse events may abate as therapy is continued and some degree of tolerance is developed, but others may be expected to remain throughout therapy.

In all patients for whom dosing information was available (n=191) from the open-label and double-blind studies involving immediate-release oxycodone, the following adverse events were recorded in oxycodone treated patients with an incidence ≥3%. In descending order of frequency they were: nausea, constipation, vomiting, headache, pruritus, insomnia, dizziness, asthenia, and somnolence.

The following adverse experiences occurred in less than 3% of patients involved in clinical trials with oxycodone:

abdominal pain, accidental injury, allergic reaction, back pain, chills and fever, fever, flu syndrome, infection, neck pain, pain, photosensitivity reaction, and sepsis. Body as a Whole:

: deep thrombophlebitis, heart failure, hemorrhage, hypotension, migraine, palpitation, and tachycardia. Cardiovascular

: anorexia, diarrhea, dyspepsia, dysphagia, gingivitis, glossitis, and nausea and vomiting. Digestive

: anemia and leukopenia. Hemic and Lymphatic

: edema, gout, hyperglycemia, iron deficiency anemia and peripheral edema. Metabolic and Nutritional

: arthralgia, arthritis, bone pain, myalgia and pathological fracture. Musculoskeletal

agitation, anxiety, confusion, dry mouth, hypertonia, hypesthesia, nervousness, neuralgia, personality disorder, tremor, and vasodilation. Nervous:

: bronchitis, cough increased, dyspnea, epistaxis, laryngismus, lung disorder, pharyngitis, rhinitis, and sinusitis. Respiratory

: herpes simplex, rash, sweating, and urticaria. Skin and Appendages

: amblyopia. Special Senses

: urinary tract infection Urogenital

7 DRUG INTERACTIONS

7.1 CNS Depressants

Other central nervous system (CNS) depressants including sedatives, hypnotics, general anesthetics, antiemetics, phenothiazines, or other tranquilizers or alcohol increases the risk of respiratory depression, hypotension, profound sedation, or coma. Use oxycodone hydrochloride with caution and in reduced dosages in patients taking these agents.

7.2 Muscle Relaxants

Oxycodone hydrochloride may enhance the neuromuscular blocking action of skeletal muscle relaxants and produce an increased degree of respiratory depression.

7.3 Mixed Agonist/Antagonist Opioid Analgesics

Do not administer mixed agonist/antagonist analgesics (i.e., pentazocine, nalbuphine, butorphanol and buprenorphine) to patients who have received or are receiving a course of therapy with a pure opioid agonist analgesic such as oxycodone hydrochloride. In these patients, mixed agonist/antagonist analgesics may reduce the analgesic effect and/or may precipitate withdrawal symptoms.

7.4 Agents Affecting Cytochrome P450 Enzymes

CYP3A4 Inhibitors

A published study showed that the co-administration with voriconazole, a CYP3A4 inhibitor, significantly increased the plasma concentrations of oxycodone. Inhibition of CYP3A4 activity by its inhibitors, such as macrolide antibiotics (e.g., erythromycin), azole-antifungal agents (e.g., ketoconazole), and protease inhibitors (e.g., ritonavir), may prolong opioid effects. If co-administration is necessary, caution is advised when initiating therapy with, currently taking, or discontinuing CYP3A4 inhibitors. Evaluate these patients at frequent intervals and consider dose adjustments until stable drug effects are achieved. [ ] see Clinical Pharmacology (12.3)

CYP3A4 Inducers

A published study showed that the co-administration of rifampin, a drug metabolizing enzyme inducer, significantly decreased plasma oxycodone concentrations. Induction of CYP3A4 activity by its inducers, such as rifampin, carbamazepine, and phenytoin, may lead to a lack of efficacy or, possibly, development of an abstinence syndrome in a patient who had developed physical dependence to oxycodone. If co-administration is necessary, caution is advised when initiating therapy with, currently taking, or discontinuing CYP3A4 inducers. Evaluate these patients at frequent intervals and consider dose adjustments until stable drug effects are achieved. [ ] see Clinical Pharmacology (12.3)

CYP2D6 Inhibitors

Oxycodone is metabolized in part to oxymorphone via the cytochrome p450 isoenzyme CYP2D6. While this pathway may be blocked by a variety of drugs (e.g., certain cardiovascular drugs and antidepressants), such blockade has not yet been shown to be of clinical significance with this agent. However, clinicians should be aware of this possible interaction.

7.5 Monoamine Oxidase Inhibitors (MAOIs)

No specific interaction between oxycodone and monoamine oxidase inhibitors has been observed, but caution in the use of any opioid in patients taking this class of drugs is appropriate.

7.6 Anticholinergics

Anticholinergics or other medications with anticholinergic activity when used concurrently with opioid analgesics may result in increased risk of urinary retention and/or severe constipation, which may lead to paralytic ileus.

8 USE IN SPECIFIC POPULATIONS

8.1 Pregnancy

Pregnancy Category B: There are no adequate and well-controlled studies of oxycodone use during pregnancy. Based on limited human data in the literature, oxycodone does not appear to increase the risk of congenital malformations. Because animal reproduction studies are not always predictive of human response, oxycodone should be used during pregnancy only if clearly needed.

Teratogenic effects

Reproduction studies in Sprague-Dawley rats and New Zealand rabbits revealed that when oxycodone was administered orally at doses up to 16 mg/kg (approximately 2 times the daily oral dose of 90 mg for adults on a mg/m basis) and 25 mg/kg (approximately 5 times the daily oral dose of 90 mg on a mg/m basis), respectively, was not teratogenic or embryo-fetal toxic.^2^2

Nonteratogenic effects

Neonates whose mothers have taken oxycodone chronically may exhibit respiratory depression and/or withdrawal symptoms, either at birth and/or in the nursery.

8.2 Labor and Delivery

Opioids cross the placenta and may produce respiratory depression and psycho-physiologic effects in neonates. Oxycodone hydrochloride is not recommended for use in women during and immediately prior to labor. Occasionally, opioid analgesics may prolong labor through actions which temporarily reduce the strength, duration and frequency of uterine contractions. However this effect is not consistent and may be offset by an increased rate of cervical dilatation, which tends to shorten labor. Closely observe neonates whose mothers received opioid analgesics during labor for signs of respiratory depression. Have a specific opioid antagonist, such as naloxone or nalmefene, available for reversal of opioid-induced respiratory depression in the neonate.

8.3 Nursing Mothers

Low levels of oxycodone have been detected in maternal milk. The amount of oxycodone hydrochloride delivered to the infant depends on the plasma concentration of the mother, the amount of milk ingested by the infant, and the extent of first-pass metabolism. Because of the potential for serious adverse reactions in nursing infants from oxycodone hydrochloride including respiratory depression, sedation and possibly withdrawal symptoms, upon cessation of oxycodone hydrochloride administration to the mother, decide whether to discontinue nursing or to discontinue the drug, taking into account the importance of the drug to the mother.

8.4 Pediatric Use

The safety and effectiveness and the pharmacokinetics of oxycodone hydrochloride oral solution in pediatric patients below the age of 18 have not been established.

8.5 Geriatric Use

Elderly patients (aged 65 years or older) may have increased sensitivity to oxycodone hydrochloride. In general, use caution when selecting a dose for an elderly patient, usually starting at the low end of the dosing range, reflecting the greater frequency of decreased hepatic, renal, or cardiac function and of concomitant disease or other drug therapy.

8.6 Hepatic Impairment

Since oxycodone is extensively metabolized, its clearance may be decreased in patients with hepatic impairment. Follow a conservative approach to dose initiation in patients with hepatic impairment, monitor patients closely and adjust the dose based on clinical response.

8.7 Renal Impairment

Information from oxycodone tablets indicate that patients with renal impairment (defined as a creatinine clearance <60 mL/min) had higher plasma concentrations of oxycodone than subjects with normal renal function. Use a conservative approach to dose initiation in patients with renal impairment, monitor patients closely and adjust the dose based on clinical response.

9 DRUG ABUSE AND DEPENDENCE

9.1 Controlled Substance

Oxycodone hydrochloride is a mu-agonist opioid and is a Schedule II controlled substance. Oxycodone hydrochloride, like other opioids used in analgesia, can be abused and is subject to criminal diversion.

9.2 Abuse

Drug addiction is characterized by compulsive use, use for non-medical purposes, and continued use despite harm or risk of harm. Drug addiction is a treatable disease, utilizing a multidisciplinary approach, but relapse is common.

"Drug-seeking" behavior is very common in addicts and drug abusers. Drug seeking tactics include emergency calls or visits near the end of office hours, refusal to undergo appropriate examination, testing or referral, repeated "loss" of prescriptions, tampering with prescriptions and reluctance to provide prior medical records or contact information for other treating physician(s). "Doctor shopping" to obtain additional prescriptions is common among drug abusers and people suffering from untreated addiction.

Abuse and addiction are separate and distinct from physical dependence and tolerance. Physicians should be aware that addiction may not be accompanied by concurrent tolerance and symptoms of physical dependence. The converse is also true. In addition, abuse of opioids can occur in the absence of true addiction and is characterized by misuse for nonmedical purposes, often in combination with other psychoactive substances. Careful recordkeeping of prescribing information, including quantity, frequency, and renewal requests is strongly advised.

Oxycodone hydrochloride is intended for oral use only. Abuse of oxycodone hydrochloride poses a risk of overdose and death. The risk is increased with concurrent abuse of alcohol and other substances. Parenteral drug abuse is commonly associated with transmission of infectious diseases such as hepatitis and HIV.

Proper assessment of the patient, proper prescribing practices, periodic reevaluation of therapy, and proper dispensing and storage are appropriate measures that help to limit abuse of opioid drugs.

Infants born to mothers physically dependent on opioids will also be physically dependent and may exhibit respiratory difficulties and withdrawal symptoms.[See Use in Specific Populations (8.2)]

9.3 Dependence

Tolerance is the need for increasing doses of opioids to maintain a defined effect such as analgesia (in the absence of disease progression or other external factors). Physical dependence is manifested by withdrawal symptoms after abrupt discontinuation of a drug or upon administration of an antagonist. Physical dependence and tolerance are not unusual during chronic opioid therapy.

The opioid abstinence or withdrawal syndrome is characterized by some or all of the following: restlessness, lacrimation, rhinorrhea, yawning, perspiration, chills, myalgia, and mydriasis. Other symptoms also may develop, including irritability, anxiety, backache, joint pain, weakness, abdominal cramps, insomnia, nausea, anorexia, vomiting, diarrhea, or increased blood pressure, respiratory rate, or heart rate.

In general, taper opioids rather than abruptly discontinue. [See Dosage and Administration (2)]

10 OVERDOSAGE

10.1 Symptoms

Acute overdosage with oxycodone hydrochloride is manifested by respiratory depression (a decrease in respiratory rate and/or tidal volume, Cheyne-Stokes respiration, cyanosis), extreme somnolence progressing to stupor or coma, skeletal muscle flaccidity, cold and clammy skin, constricted pupils, and, in some cases, pulmonary edema, bradycardia, hypotension, cardiac arrest and death.

Oxycodone hydrochloride may cause miosis, even in total darkness. Pinpoint pupils are a sign of opioid overdose but are not pathognomonic (e.g., pontine lesions of hemorrhagic or ischemic origin may produce similar findings). Marked mydriasis rather than miosis may be seen with hypoxia in overdose situations. [See Clinical Pharmacology (12)]

10.2 Treatment

Give primary attention to reestablishment of a patent airway and institution of assisted or controlled ventilation. Employ supportive measures (including oxygen and vasopressors) in the management of circulatory shock and pulmonary edema accompanying overdose as indicated. Cardiac arrest or arrhythmias may require cardiac massage or defibrillation.

The pure opioid antagonists, naloxone or nalmefene, are specific antidotes to respiratory depression resulting from opioid overdose. Since the duration of reversal is expected to be less than the duration of action of oxycodone hydrochloride, carefully monitor the patient until spontaneous respiration is reliably reestablished. If the response to opioid antagonists is suboptimal or only brief in nature, administer additional antagonist as directed by the manufacturer of the product.

Do not administer opioid antagonists in the absence of clinically significant respiratory or circulatory depression secondary to oxycodone overdose. Administer such agents cautiously to persons who are known, or suspected to be physically dependent on oxycodone. In such cases, an abrupt or complete reversal of opioid effects may precipitate an acute abstinence syndrome.

In an individual physically dependent on opioids, administration of the usual dose of the antagonist will precipitate an acute withdrawal syndrome. The severity of the withdrawal symptoms experienced will depend on the degree of physical dependence and the dose of the antagonist administered. Reserve use of an opioid antagonist for cases where such treatment is clearly needed. If it is necessary to treat serious respiratory depression in the physically dependent patient, initiate administration of the antagonist with care and titrate with smaller than usual doses.

11 DESCRIPTION

Oxycodone hydrochloride is a white, odorless crystalline powder derived from the opium alkaloid, thebaine. It is soluble in water and slightly soluble in alcohol.

Chemically, oxycodone hydrochloride is (5 , ,13 ,14) 4, 5α-epoxy-14-hydroxy-3-methoxy-17- methylmorphinan-6-one hydrochloride with a molecular mass of 351.82. R 9RSS-

100 mg per 5 mL (20 mg/mL): Each 1 mL of oral clear, light yellow to yellow solution contains 20 mg of oxycodone hydrochloride, USP and the following inactive ingredients: anhydrous citric acid, artificial strawberry flavor, disodium edetate, D&C Yellow #10, purified water, sodium benzoate, sorbitol, and sucralose.

12 CLINICAL PHARMACOLOGY

12.1 Mechanism of Action

Oxycodone hydrochloride, a pure opioid agonist, is relatively selective for the mu receptor, although it can interact with other opioid receptors at higher doses. In addition to analgesia, the widely diverse effects of oxycodone hydrochloride include drowsiness, changes in mood, respiratory depression, decreased gastrointestinal motility, nausea, vomiting, and alterations of the endocrine and autonomic nervous system.

Effects of the Central Nervous System (CNS)

The principal therapeutic action of oxycodone hydrochloride is analgesia. Although the precise mechanism of the analgesic action is unknown, specific CNS opioid receptors for endogenous compounds with oxycodone hydrochloride-like activity have been identified throughout the brain and spinal cord and are likely to play a role in the expression and perception of analgesic effects. In common with other opioids, oxycodone hydrochloride causes respiratory depression, in part by a direct effect on the brainstem respiratory centers. Oxycodone and related opioids depress the cough reflex by direct effect on the cough center in the medulla.

Oxycodone causes miosis, even in total darkness.

Effects on the Gastrointestinal Tract And Other Smooth Muscle

Gastric, biliary and pancreatic secretions are decreased by oxycodone hydrochloride. Oxycodone hydrochloride, like other opioid analgesics, produces some degree of nausea and vomiting which is caused by direct stimulation of the chemoreceptor trigger zone (CTZ) located in the medulla. The frequency and severity of emesis gradually diminishes with time. Oxycodone hydrochloride may cause a decrease in the secretion of hydrochloric acid in the stomach, may reduce motility, while increasing the tone in the antrum of the stomach and duodenum. Digestion of food in the small intestine is delayed and propulsive contractions are decreased. Propulsive peristaltic waves in the colon are decreased, while tone may be increased to the point of spasm. The end result may be constipation. Oxycodone hydrochloride may also cause spasm of the sphincter of Oddi and transient elevations in serum amylase.

Effects on the Cardiovascular System

In therapeutic doses, oxycodone hydrochloride, produces peripheral vasodilatation (arteriolar and venous), decreased peripheral resistance, and inhibits baroreceptor reflexes. Manifestations of histamine release and/or peripheral vasodilatation may include pruritus, flushing, red eyes, sweating, and/or orthostatic hypotension. Caution should be used in hypovolemic patients, such as those suffering acute myocardial infarction, because oxycodone may cause or further aggravate their hypotension. Caution should also be used in patients with cor pulmonale who have received therapeutic doses of opioids.

Endocrine System

Opioid agonists have been shown to have a variety of effects on the secretion of hormones. Opioids inhibit the secretion of ACTH, cortisol, and luteinizing hormone (LH) in humans. They also stimulate prolactin, growth hormone (GH) secretion, and pancreatic secretion of insulin and glucagon in humans and other species, rats and dogs. Thyroid stimulating hormone (TSH) has been shown to be both inhibited and stimulated by opioids.

Immune System

Opioids have been shown to have a variety of effects on components of the immune system in and animal models. The clinical significance of these findings is unknown. in vitro

12.3 Pharmacokinetics

The activity of oxycodone hydrochloride is primarily due to the parent drug oxycodone.

The oral bioavailability of oxycodone is 60% to 87%. Oxycodone is extensively metabolized and eliminated primarily in the urine as both conjugated and unconjugated parent and its metabolites. The apparent elimination half-life of oxycodone is approximately 4 hours.

Absorption

About 60 to 87% of an oral dose reaches the systemic circulation in comparison to a parenteral dose. This high oral bioavailability (compared to other opioids) is due to lower pre-systemic and/or first-pass metabolism of oxycodone.

Food Effects

When oxycodone capsules are administered with a high-fat meal, mean AUC values are increased by 23% and peak concentrations are decreased by 14%. Food causes a delay in T (1 to 3 hours). Similar effects of food are expected with the oral solution.max

Distribution

Following intravenous administration, the volume of distribution (Vss) for oxycodone was 2.6 L/kg. Plasma protein binding of oxycodone at 37°C and a pH of 7.4 was about 45%. Oxycodone has been found in breast milk.

Metabolism

Oxycodone hydrochloride is extensively metabolized by multiple metabolic pathways to noroxycodone, oxymorphone, and noroxymorphone, which are subsequently glucuronidated. CYP3A4 mediated N- demethylation to noroxycodone is the primary metabolic pathway of oxycodone with a less contribution from CYP2D6 mediated O-demethylation to oxymorphone. Therefore, the formation of these and related metabolites can, in theory, be affected by other drugs. The major circulating metabolite is noroxycodone with an AUC ratio of 0.6 relative to that of oxycodone. Noroxycodone is reported to be a considerably weaker analgesic than oxycodone. Oxymorphone, although possessing analgesic activity, is present in the plasma only in low concentrations. The correlation between oxymorphone concentrations and opioid effects was much less than that seen with oxycodone plasma concentrations. The analgesic activity profile of other metabolites is not known.

Excretion

Oxycodone and its metabolites are excreted primarily via the kidney. The amounts measured in the urine have been reported as follows: free oxycodone up to 19%; conjugated oxycodone up to 50%; free oxymorphone 0%; conjugated oxymorphone < 14%; both free and conjugated noroxycodone have been found in the urine but not quantified. The total plasma clearance was 0.8 L/min for adults.

Apparent elimination half-life of oxycodone following the administration of oxycodone is approximately 4 hours.

Special Populations

Information obtained from oxycodone tablets indicate that the plasma concentrations of oxycodone did not appear to be increased in patients over of the age of 65. Elderly:

Information obtained from oxycodone tablets support the lack of gender effect on the pharmacokinetics of oxycodone. Gender:

Information obtained from oxycodone tablets indicate that patients with renal impairment (defined as creatinine clearance < 60 mL/min) had higher plasma concentrations of oxycodone than subjects with normal renal function. Renal Impairment:

Since oxycodone is extensively metabolized, its clearance may be decreased in patients with hepatic impairment. Hepatic Impairment:

Drug-Drug Interactions

: CYP3A4 is the major enzyme involved in noroxycodone formation. A published study showed that the co-administration of voriconazole, a CYP3A4 inhibitor, increased oxycodone AUC and C by 3.6 and 1.7 fold, respectively. CYP3A4 Inhibitorsmax

: A published study showed that the co-administration of rifampin, a drug metabolizing enzyme inducer, decreased oxycodone AUC and C values by 86% and 63%, respectively. CYP3A4 Inducersmax

: Oxycodone is metabolized in part to oxymorphone via the cytochrome p450 isoenzyme CYP2D6. While this pathway may be blocked by a variety of drugs (e.g., certain cardiovascular drugs and antidepressants), such blockade has not yet been shown to be of clinical significance with this agent. CYP2D6 Inhibitors

13 NONCLINICAL TOXICOLOGY

13.1 Carcinogenesis, Mutagenesis, Impairment of Fertility

Carcinogenesis

Studies of oxycodone hydrochloride to evaluate its carcinogenic potential have not been conducted.

Mutagenesis

Oxycodone hydrochloride was genotoxic in an mouse lymphoma assay in the presence of metabolic activation. There was no evidence of genotoxic potential in an bacterial reverse mutation assay (and) and in an assay for chromosomal aberrations (mouse bone marrow micronucleus assay). in vitroin vitro Salmonella typhimurium Escherichia coliin vivo

Impairment of Fertility

The potential effects of oxycodone on male and female fertility have not been evaluated.

16 HOW SUPPLIED/STORAGE AND HANDLING

NDC:17856-0393-1 1 mL in a SYRINGE, PLASTIC

17 PATIENT COUNSELING INFORMATION

See Medication Guide

Provide the following information to patients receiving oxycodone hydrochloride or their caregivers:

- Advise patients that oxycodone hydrochloride is a narcotic pain reliever, and should be taken only as directed.
- Advise patients how to measure and take the correct dose of oxycodone hydrochloride oral solution, and to always use the enclosed syringe when administering oxycodone hydrochloride oral solution 100 mg per 5 mL (20 mg/mL) to ensure the dose is measured and administered accurately.
- Advise patients whenever the prescribed concentration is changed to avoid dosing errors which could result in accidental overdose and death.
- Advise patients that the 100 mg per 5 mL (20 mg/mL) formulation is only for patients who are already receiving opioid-therapy and have demonstrated opioid-tolerance and that sharing this medication can result in fatal overdose and death, particularly in persons who have not had previous exposure to opioids.
- Advise patients not to adjust the dose of oxycodone hydrochloride without consulting with a physician or other healthcare professional.
- Advise patients that oxycodone hydrochloride may cause drowsiness, dizziness, or lightheadedness and may impair mental and/or physical ability required for the performance of potentially hazardous tasks (e.g., driving, operating machinery). Advise patients started on oxycodone hydrochloride or patients whose dose has been adjusted to refrain from any potentially dangerous activity until it is established that they are not adversely affected.
- Advise patients that oxycodone hydrochloride will add to the effect of alcohol and other CNS depressants (such as antihistamines, sedatives, hypnotics, tranquilizers, general anesthetics, phenothiazines, other opioids, and monoamine oxidase [MAO] inhibitors).
- Instruct patients not to combine oxycodone hydrochloride with central nervous system depressants (sleep aids, tranquilizers) except by the orders of the prescribing physician, and not to combine with alcohol because dangerous additive effects may occur, resulting in serious injury or death.
- Instruct women of childbearing potential who become or are planning to become pregnant to consult a physician prior to initiating or continuing therapy with oxycodone hydrochloride.
- Advise patients that safe use in pregnancy has not been established and that prolonged use of opioid analgesics during pregnancy may cause fetal-neonatal physical dependence, and neonatal withdrawal may occur.
- If patients have been receiving treatment with oxycodone hydrochloride for more than a few weeks and cessation of therapy is indicated, counsel them on the importance of safely tapering the dose and that abruptly discontinuing the medication could precipitate withdrawal symptoms. Provide a dose schedule to accomplish a gradual discontinuation of the medication.
- Advise patients that oxycodone hydrochloride is a potential drug of abuse. They must protect it from theft. It should never be given to anyone other than the individual for whom it was prescribed.
- Instruct patients to keep oxycodone hydrochloride in a secure place out of the reach of children. When oxycodone hydrochloride is no longer needed, the unused solution should be destroyed by flushing down the toilet.
- Advise patients taking oxycodone hydrochloride of the potential for severe constipation; appropriate laxatives and/or stool softeners as well as other appropriate treatments should be initiated from the onset of opioid therapy.
- Advise patients of the most common adverse events that may occur while taking oxycodone hydrochloride: constipation, nausea, somnolence, lightheadedness, dizziness, sedation, vomiting, and sweating.
- Advise patients to call 911 or the local Poison Control center, and get emergency help immediately if they take more oxycodone than prescribed, or overdose.
- Advise patients, that if they miss a dose, to take the missed dose as soon as possible. If it is almost time for the next dose, skip the missed dose and go back to their regular dosing schedule. Do not take two doses at once unless instructed by their doctor.

MEDICATION GUIDE

Oxycodone Hydrochloride USP (ox-ee-CO-dohn) CII

Oral Solution

BOXED WARNING

IMPORTANT: Keep oxycodone hydrochloride oral solution in a safe place away from children. Accidental use by a child is a medical emergency and can cause death. If a child accidentally takes oxycodone hydrochloride oral solution, get emergency help right away.

Read the Medication Guide that comes with oxycodone hydrochloride oral solution before you start taking it and each time you get a new prescription. There may be new information. This Medication Guide does not take the place of talking to your healthcare provider about your medical condition or your treatment.

What is the Most Important Information I Should Know About Oxycodone Hydrochloride Oral Solution?

Oxycodone hydrochloride oral solution can cause serious side effects, including, death.

1. If you take the wrong dose or strength of oxycodone hydrochloride oral solution, you could overdose and die. Take oxycodone hydrochloride oral solution exactly as prescribed by your healthcare provider.
2. It is especially important when you take oxycodone hydrochloride oral solution that you know exactly what dose and strength to take, and the right way to measure your medicine. Your healthcare provider or pharmacist should show you the right way to measure your medicine.
3. Always use the oral syringe provided with oxycodone hydrochloride oral solution, 100 mg per 5 mL (20 mg per mL) to help make sure you measure the right amount. Oral Syringe.
4. Using alcohol with oxycodone hydrochloride oral solution may increase your risk of dangerous side effects, including death. Do not drink alcohol.
5. Opioid tolerant means that you take another opioid medicine for your constant (around the clock) pain and your body is used to it. Opioid Tolerance. Do not take oxycodone hydrochloride oral solution, 100 mg per 5 mL (20 mg per mL), unless you are “opioid tolerant.”

What is Oxycodone Hydrochloride Oral Solution?

Oxycodone hydrochloride oral solution is in a group of drugs called narcotic pain relievers. Oxycodone hydrochloride oral solution is only for adults who have moderate to severe pain.

- A prescription medicine that is used to manage moderate to severe pain that is expected to last a short period of time (acute), and pain that continues around-the-clock and is expected to last for a long period of time (chronic).
- Oxycodone hydrochloride oral solution is a federally controlled substance (CII) because it is a strong opioid pain medicine that can be abused by people who abuse prescription medicines or street drugs.
- Prevent theft, misuse or abuse. Keep oxycodone hydrochloride oral solution in a safe place to keep it from being stolen. Oxycodone hydrochloride oral solution can be a target for people who misuse or abuse prescription medicines or street drugs.
- Never give oxycodone hydrochloride oral solution to anyone else, even if they have the same symptoms you have. It may harm them or even cause death.
- Selling or giving away this medicine is against the law.
- It is not known if oxycodone hydrochloride oral solution is safe and effective in children under age 18 years of age.
- Oxycodone hydrochloride 100 mg per 5 mL (20 mg per mL) oral solution is only for adults with moderate to severe pain who are already using an opioid narcotic pain medicine and have been using this medicine continuously for several weeks or longer.

Who Should Not Take Oxycodone Hydrochloride Oral Solution?

Do not take oxycodone hydrochloride oral solution if you:

- See the end of this Medication Guide for a complete list of ingredients in oxycodone hydrochloride oral solution. are allergic to oxycodone, oxycodone salts, or any of the ingredients in oxycodone hydrochloride oral solution.
- are having breathing problems and there is no emergency medical equipment nearby
- are having an asthma attack or have severe asthma, trouble breathing, or lung problems
- have a bowel blockage called paralytic ileus

What Should I Tell My Healthcare Provider Before Taking Oxycodone Hydrochloride Oral Solution?

Before taking oxycodone hydrochloride oral solution, tell your healthcare provider if you:

- have trouble breathing or lung problems
- have had a head injury
- have liver or kidney problems
- have adrenal gland problems, such as Addison’s disease
- have severe scoliosis that affects your breathing
- have thyroid problems
- have problems urinating or enlargement of your prostate
- have or had convulsions or seizures
- have a past or present drinking problems or alcoholism
- have hallucinations (seeing or hearing things that are not really there) or other severe mental problems
- have constipation or other bowel problems
- have problems with your pancreas or gallbladder
- have past or present substance abuse or drug addiction
- have any other medical conditions
- are pregnant or plan to become pregnant. It is not known if oxycodone hydrochloride oral solution will harm your unborn baby. Talk to your healthcare provider if you are pregnant or plan to become pregnant.

If you take oxycodone hydrochloride oral solution regularly before your baby is born, your newborn baby may have signs of withdrawal because their body has become used to the medicine. Signs of withdrawal in a newborn baby can include:

● irritability

● vomiting

● being very active

● diarrhea or more stools than normal

● problems sleeping

● weight loss

● high pitched cry

● shaking (tremors)

If you are taking oxycodone hydrochloride oral solution right before your baby is born, your baby could have breathing problems.

- are breast-feeding or plan to breastfeed. Some oxycodone hydrochloride oral solution passes into your breast milk. A nursing baby could become very sleepy or have difficulty breathing or feeding well. If you stop breastfeeding, your baby may have withdrawal symptoms. See the list of withdrawal symptoms above. You and your healthcare provider should decide if you will take oxycodone hydrochloride oral solution or breastfeed.

including prescription and non-prescription medicines, vitamins, and herbal supplements. Sometimes the doses of medicines that you take with oxycodone hydrochloride oral solution may need to be changed if used together. Be especially careful about taking other medicines that make you sleepy such as: Tell your healthcare provider about all the medicines you take,

sleeping pills | anti-anxiety medicines
other pain medicines | antidepressants
anti-nausea medicines | monoamine oxidase inhibitors (MAOIs)
tranquilizers | muscle relaxants
antihistamines | anticholinergic medicines

Ask your healthcare provider if you are not sure if your medicine is one listed above.

- Do not take other medicines while using oxycodone hydrochloride oral solution until you have talked with your healthcare provider or pharmacist. They will tell you if it is safe to take other medicines with oxycodone hydrochloride oral solution.

Know the medicines you take. Keep a list of them and show it to your healthcare provider and pharmacist when you get a new medicine.

How Should I Take Oxycodone Hydrochloride Oral Solution?

- See “What is the most important information I should know about oxycodone hydrochloride oral solution?”
- . Do not change your dose unless your healthcare provider tells you to. Your healthcare provider may change your dose after seeing how the medicine affects you. Call your healthcare provider if your pain is not well controlled with your prescribed dose of oxycodone hydrochloride oral solution. Take oxycodone hydrochloride oral solution exactly as prescribed
- Always use the oral dropper provided with your oxycodone hydrochloride oral solution, 100 mg per 5 mL (20 mg per mL), to help make sure you measure the right amount. See the Patient Instructions for Use at the end of this Medication Guide for information about how to measure your dose the right way. Ask your healthcare provider or pharmacist if you are not sure what dose of oxycodone hydrochloride oral solution you should take or if you are not sure how to use the oral syringe. Make sure you understand exactly how to measure your dose.
- . If you have been taking oxycodone hydrochloride oral solution for more than a few weeks, stopping it suddenly can make you sick with withdrawal symptoms (for example, nausea, vomiting, diarrhea, anxiety, and shivering). If your healthcare provider decides you no longer need oxycodone hydrochloride oral solution, ask how to slowly reduce this medicine. Do not stop taking oxycodone hydrochloride oral solution without talking to your healthcare provider. Do not stop taking oxycodone hydrochloride oral solution suddenly
- If you take more oxycodone than prescribed, or overdose, call your local emergency number (such as 911) or your local Poison Control Center right away or get emergency help.
- Talk with your healthcare provider regularly about your pain to see if you still need to take oxycodone.

What Should I Avoid While Taking Oxycodone Hydrochloride Oral Solution?

- You should not drink alcohol while using oxycodone hydrochloride oral solution. Drinking alcohol with oxycodone hydrochloride oral solution may increase your risk of having dangerous side effects or death.
- especially when you start taking oxycodone hydrochloride oral solution and when your dose is changed, until you know how oxycodone hydrochloride oral solution affects you. Oxycodone can make you sleepy. Ask your healthcare provider to tell you when it is okay to do these activities. Do not drive, operate heavy machinery, or do other dangerous activities,

What are the Possible Side Effects of Oxycodone Hydrochloride Oral Solution?

Oxycodone hydrochloride oral solution can cause serious side effects, including:

- See “What is the most important information I should now about oxycodone hydrochloride oral solution?”
- Call your healthcare provider or get help right away if: Oxycodone can cause serious breathing problems that can become life-threatening, especially if oxycodone hydrochloride oral solution is used the wrong way.
  - your breathing slows down
  - you have shallow breathing (little chest movement with breathing)
  - you feel faint, dizzy, confused, or
  - you have any other unusual symptoms

These can be symptoms that you have taken too much oxycodone hydrochloride oral solution (overdose) or the dose is too high for you. These symptoms may lead to serious problems or death if not treated right away.

- This can make you feel dizzy if you get up too fast from sitting or lying down. Low blood pressure is also more likely to happen if you take other medicines that can also lower your blood pressure. Severe low blood pressure can happen if you lose blood or take certain other medicines. Oxycodone hydrochloride oral solution can cause your blood pressure to drop.
- Do not stop taking oxycodone or any other opioid without talking to your healthcare provider about how to slowly stop your medicine. You could become sick with uncomfortable withdrawal symptoms because your body has become used to these medicines. Physical dependence is not the same as drug addiction. Tell your healthcare provider if you have any of these symptoms of withdrawal while slowly stopping oxycodone: Oxycodone can cause physical dependence.

feel restless | runny nose
tearing eyes | yawning
sweating | nausea, loss of appetite, vomiting, diarrhea, stomach-area (abdominal) cramps
chills or hair on your arms “stand up” | feel irritable or anxious
muscle aches, backache | trouble sleeping
dilated pupils of your eyes | increase in your blood pressure, breathing faster, or your heart beats faster

- The chance is higher if you are or have been addicted to or abused other medicines, street drugs, or alcohol, or if you have a history of mental problems. There is a chance of abuse or addiction with oxycodone hydrochloride oral solution.
- Seizures. Oxycodone hydrochloride oral solution may cause seizures or make seizures that you already have worse.

Call your healthcare provider if you have any of the symptoms listed above.

Common side effects of oxycodone hydrochloride oral solution include:

● nausea

● dizziness

● constipation

● weakness

● vomiting

● drowsiness

● headache

● sweating

● itchiness

● lightheadedness

● trouble sleeping

Constipation (not often enough or hard bowel movements) is a very common side effect of pain medicines (opioids) including oxycodone hydrochloride oral solution. Talk to your healthcare provider about dietary changes, and the use of laxatives (medicines to treat constipation) and stool softeners to prevent or treat constipation while taking oxycodone hydrochloride oral solution.

Tell your healthcare provider if you have any side effect that bothers you or that does not go away. These are not all the possible side effects of oxycodone hydrochloride oral solution. For more information, ask your healthcare provider or pharmacist.

Call your doctor for medical advice about side effects. You may report side effects to FDA at 1-800-FDA-1088.

How Should I Store Oxycodone Hydrochloride Oral Solution?

- Store oxycodone hydrochloride oral solution in a dry area at 68° to 77°F (20° to 25°C).
- Protect oxycodone hydrochloride oral solution from moisture and light.
- After you stop taking oxycodone, flush the unused oral solution down the toilet.

Keep oxycodone hydrochloride oral solution out of the reach of children. Accidental overdose by a child is a medical emergency and can lead to death.

General Information About Oxycodone Hydrochloride Oral Solution

Medicines are sometimes prescribed for purposes other than those listed in a Medication Guide. Do not use oxycodone hydrochloride oral solution for a condition for which it was not prescribed.

Do not give your oxycodone hydrochloride oral solution to other people, even if they have the same symptoms you have. Selling or giving away oxycodone hydrochloride oral solution may harm others, may cause death, and is against the law.

This Medication Guide summarizes the most important information about oxycodone hydrochloride oral solution. If you would like more information, talk with your healthcare provider. You can ask your healthcare provider or pharmacist for information about oxycodone hydrochloride oral solution that is written for healthcare professionals.

For more information about oxycodone hydrochloride oral solution, go to www.roxane.com or call Roxane Laboratories, Inc. at 1-800-962-8364.

What are the Ingredients in Oxycodone Hydrochloride Oral Solution?

Active ingredient: oxycodone hydrochloride

anhydrous citric acid, artificial strawberry flavor, disodium edetate, D&C Yellow #10, purified water, sodium benzoate, sorbitol, and sucralose. Inactive ingredients:

This Medication Guide has been approved by the U.S. Food and Drug Administration.

Patient Instructions for Use

Oxycodone Hydrochloride Oral Solution USP, 100 mg per 5 mL (20 mg per mL)

Oral Syringe

Important information about measuring oxycodone hydrochloride oral solution

- Always use the oral syringe provided with your oxycodone hydrochloride oral solution to make sure you measure the right amount.
- Measure the dose of medicine from the widest part of the plunger. Do not measure from the narrow tip. See Figure 1.

Insert the tip of the oral syringe into the medicine bottle. Step 1.

Pull back the plunger to the line that matches the dose prescribed by your healthcare Step 2.

provider.

Remove the oral syringe from the medicine bottle. Step 3.

Take your medicine by slowly pushing the plunger until the oral syringe is empty. Step 4.

Figure 1

Figure 1

Roxane Laboratories, Inc.

Columbus, OH 43216

10007565/01 Revised October 2014

©RLI, 2014